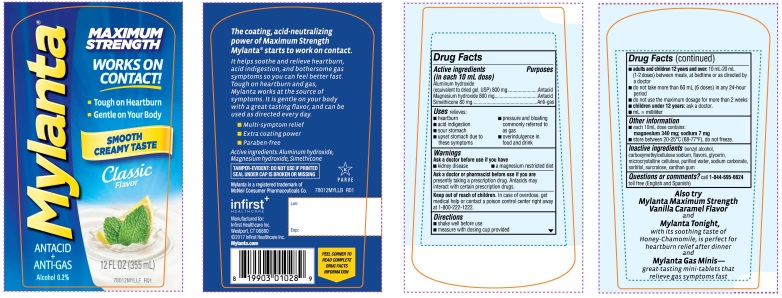 DRUG LABEL: Mylanta Maximum Strength Classic Flavor
NDC: 62372-500 | Form: SUSPENSION
Manufacturer: Infirst Healthcare Inc.
Category: otc | Type: HUMAN OTC DRUG LABEL
Date: 20241211

ACTIVE INGREDIENTS: ALUMINUM HYDROXIDE 800 mg/10 mL; MAGNESIUM HYDROXIDE 800 mg/10 mL; DIMETHICONE 80 mg/10 mL
INACTIVE INGREDIENTS: BENZYL ALCOHOL; CARBOXYMETHYLCELLULOSE SODIUM, UNSPECIFIED FORM; GLYCERIN; MICROCRYSTALLINE CELLULOSE; WATER; SODIUM CARBONATE; SORBITOL; SUCRALOSE; XANTHAN GUM

Mylanta Maximum Strength Classic Flavor 12FL OZ

Active ingredients (in each 10 mL dose)

Aluminum hydroxide

(equivalent to dried gel, USP) 800 mg

1. Magnesium hydroxide 800 mg
  Simethicone 80 mg

Purpose

Antacid

Antacid
Anti-gas

Uses

relieves:

- heartburn
- pressure and bloating commonly referred to as gas
- acid indigestion
- sour stomach
- upset stomach due to these symptoms
- overindulgence in food and drink

Warnings

Ask a doctor before use if you have
• kidney disease • a magnesium restricted diet

Ask a doctor before use if you have

• kidney disease • a magnesium restricted diet

Ask a doctor or pharmacist before use if you are

presently taking a prescription drug. Antacids may interact with certain prescription drugs.

Keep out of reach of children.

In case of overdose, get medical help or contact a poison control center right away at 1-800-222-1222

Directions

- shake well before use
- measure with dosing cup provided
- adults and children 12 years and over: 10 mL-20 mL (1-2 doses) between meals, at bedtime or as directed by a doctor
- do not take more than 60 mL (6 doses) in any 24- hour period
- do not use the maximum dosage for more than 2 weeks
- children under 12 years: ask a doctor
- mL= milliliter

Other information

- each 10 mL dose contains:

magnesium 340 mg; sodium 7 mg

- store between 20-25°C (68-77°F), do not freeze.

Inactive ingredients

benzyl alcohol, carboxymethylcellulose sodium, flavors, glycerin, microcrystalline cellulose, purified water, sodium carbonate, sorbitol, sucralose, xanthan gum

Questions or comment?

call 1-844-695-6624toll free (English and Spanish)

Principal Display Panel

MYLANTA ®

ANTACID + ANTI-GAS Alcohol 0.2%

MAXIMUM STRENGTH

WORKS ON CONTACT!

-
  -
    -
      -
        - Tough on Heartburn
        - Gentle on Your Body

SMOOTH CREAMY TASTE

Classic Flavor

12 FL OZ (355mL)

Also try Mylanta Maximum Strength Vanilla Caramel Flavor

and

Mylanta Tonight,with its soothing taste of Honey-Chamomile, is perfect for heartburn relief after dinner

and

Mylanta GasMinis ̶great- tasting mini- tablets that relieve gas symptoms fast

The coating, acid-neutralizing power of Maximum Strength Mylanta®starts to work on contact.

It helps soothe and relieve heartburn, acid indigestion, and bothersome gas symptoms so you can feel better fast.

Tough on heartburn and gas, Mylanta works at the source of symptoms. It is gentle on your body with a great-tasting flavor, and can be used as directed every day.

- Multi-symptom relief
- Extra coating power
- Paraben- free

Active ingredients: Aluminum hydroxide, Magnesium hydroxide, Simethicone

TAMPER-EVIDENT: DO NOT USE IF PRINTED SEAL UNDER CAP IS BROKEN OR MISSING

Mylanta is a registered trademark of McNeil Consumer Pharmaceuticals Co.

infirst^+

HEALTHCARE

Manufactured for:

Infirst Healthcare Inc.

Westport, CT 06880

©2017 Infirst Healthcare Inc.

Mylanta.com